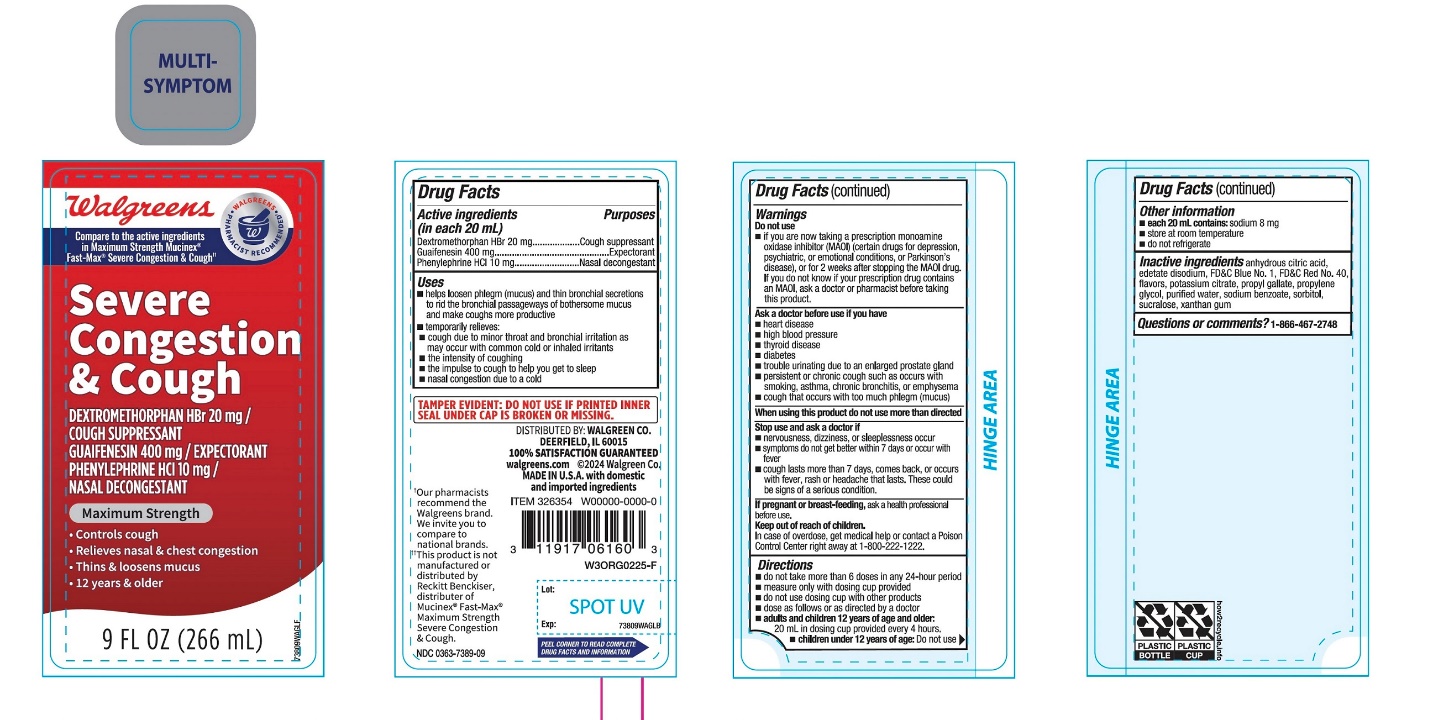 DRUG LABEL: Walgreen

NDC: 0363-7389 | Form: LIQUID
Manufacturer: WALGREENS CO.
Category: otc | Type: HUMAN OTC DRUG LABEL
Date: 20251201

ACTIVE INGREDIENTS: DEXTROMETHORPHAN HYDROBROMIDE 20 mg/20 mL; GUAIFENESIN 400 mg/20 mL; PHENYLEPHRINE HYDROCHLORIDE 10 mg/20 mL
INACTIVE INGREDIENTS: ANHYDROUS CITRIC ACID; EDETATE DISODIUM; FD&C BLUE NO. 1; FD&C RED NO. 40; POTASSIUM CITRATE; PROPYLENE GLYCOL; PROPYL GALLATE; WATER; SODIUM BENZOATE; SORBITOL; SUCRALOSE; XANTHAN GUM

Walgreen Maximum Strength Severe Congestion & Cough Drug Facts

Active ingredients (in each 20 mL)

Dextromethorphan HBr 20 mg

Guaifenesin 400 mg

Phenylephrine HCl 10 mg

Purposes

Cough suppressant

Expectorant

Nasal Decongestant

Uses

- helps loosen phlegm (mucus) and thin bronchial secretions to rid the bronchial passageways of bothersome mucus and make coughs more productive
- temporarily relieves:
  - cough due to minor throat and bronchial irritation as may occur with the common cold or inhaled irritants
  - the intensity of coughing
  - the impulse to cough to help you get to sleep
  - nasal congestion due to a cold

Warnings

Do not use

- if you are now taking a prescription monoamine oxidase inhibitor (MAOI) (certain drugs for depression, psychiatric or emotional conditions, or Parkinson's disease), or for 2 weeks after stopping the MAOI drug. If you do not know if your prescription drug contains an MAOI, ask a doctor or pharmacist before taking this product.

Ask a doctor before use if you have

- heart disease
- high blood pressure
- thyroid disease
- diabetes
- trouble urinating due to an enlarged prostate gland
- persistent or chronic cough such as occurs with smoking, asthma, chronic bronchitis or emphysema
- cough that occurs with too much phlegm (mucus)

When using this product,

do not use more than directed.

Stop use and ask a doctor if

- nervousness, dizziness or sleeplessness occur
- symptoms do not get better within 7 days or occur with a fever
- cough comes back, or occurs with rash or persistent headache. These could be signs of a serious condition.

If pregnant or breast-feeding,

ask a health professional before use.

Keep out of reach of children.

In case of overdose, get medical help or contact a Poison Control Center right away at 1-800-222-1222.

Directions

- do not take more than 6 doses in a 24-hour period
- measure only with dosing cup provided.
- do not use dosing cup with other products
- dose as follows or as directed by a doctor
- adults and children 12 years of age and older:20 mL in dosing cup provided every 4 hours
- children under 12 years of age:Do not use

Other information

- each 20 mL contains: sodium 8 mg
- low sodium
- store at room temperature
- do not refrigerate

Inactive ingredients

anhydrous citric acid, edetate disodium, FD&C Blue No. 1, FD&C Red No. 40, flavor, potassium citrate, propylene glycol, propyl gallate, purified water, sodium benzoate, sorbitol, sucralose, xanthan gum

Questions or comments?

1-866-467-2748

Principal Display Panel

Compare to Mucinex® Fast-Max® Maximum Strength Severe Congestion & Cough active ingredients*

NDC 0363-7389-09

Maximum Strength

Severe Congestion and Cough

Dextromethorphan HBr - Cough Suppressant

Guaifenesin - Expectorant

Phenylephrine HCI - Nasal Decongestant

- Controls Cough
- Relieves Nasal & Chest Congestion
- Thins & Loosens Mucus

For Ages 12 +

9 FL OZ (266 mL)

TAMPER EVIDENT: DO NOT USE IF PRINTED INNER SEAL UNDER CAP IS BROKEN OR MISSING.

PEEL CORNER TO READ COMPLETE DRUG FACTS AND INFORMATION

Distributed by:

*This product is not manufactured or distributed by Reckitt Benckiser, the distributor of Mucinex® Fast-Max® Maximum Strength Severe Congestion & Cough.